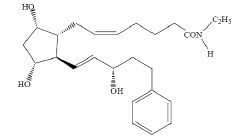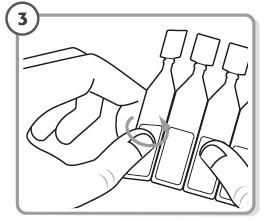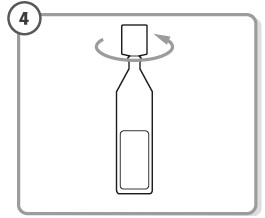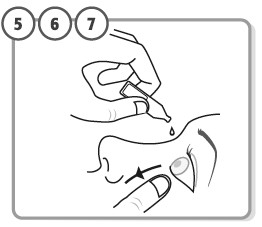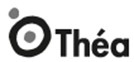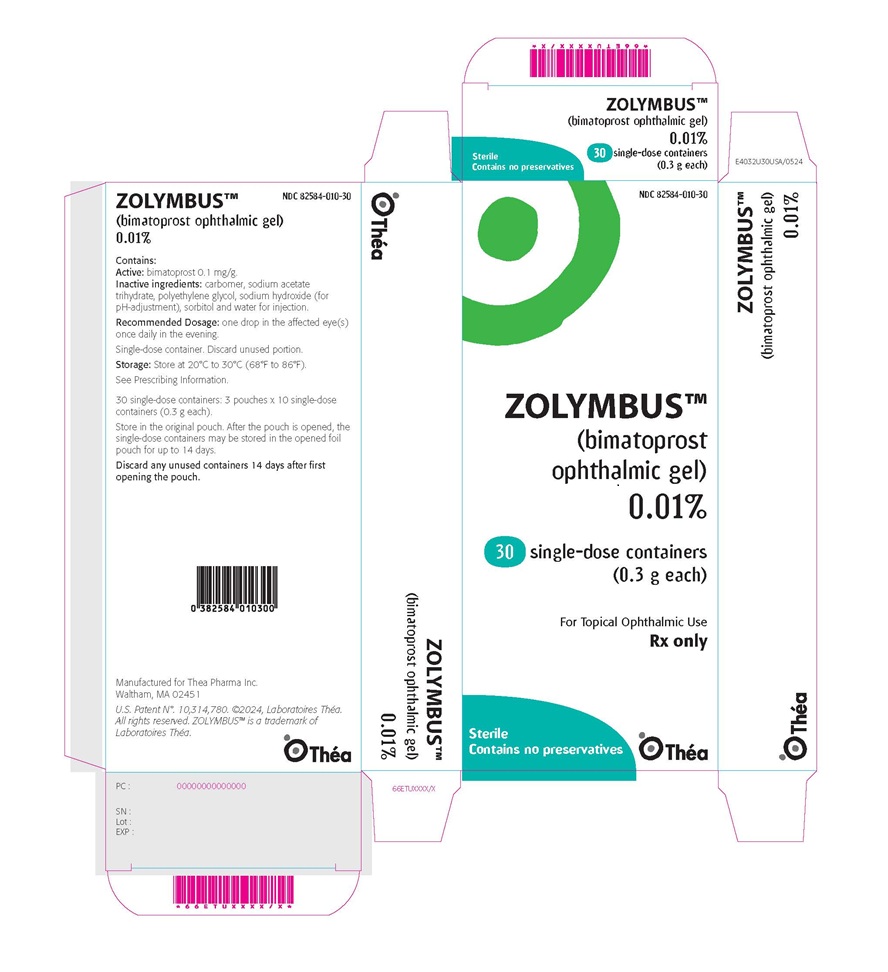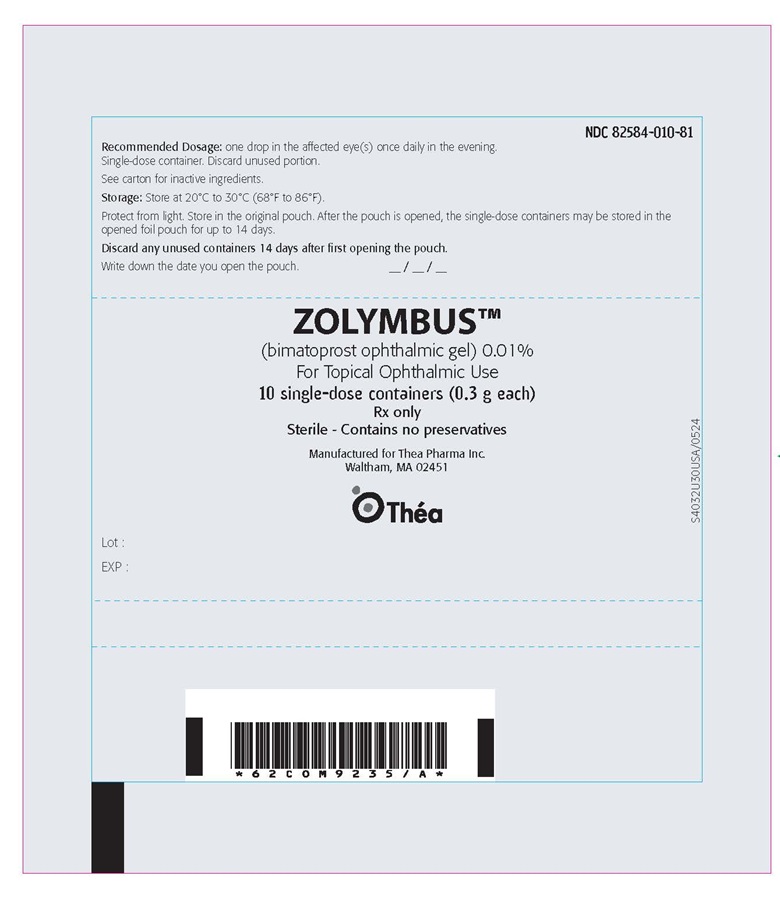 DRUG LABEL: ZOLYMBUS
NDC: 82584-010 | Form: GEL
Manufacturer: Thea Pharma Inc.
Category: prescription | Type: HUMAN PRESCRIPTION DRUG LABEL
Date: 20260225

ACTIVE INGREDIENTS: BIMATOPROST 0.1 mg/1 g
INACTIVE INGREDIENTS: CARBOMER HOMOPOLYMER TYPE B (ALLYL PENTAERYTHRITOL CROSSLINKED); POLYETHYLENE GLYCOL 4000; SODIUM ACETATE; SODIUM HYDROXIDE; SORBITOL; WATER

HIGHLIGHTS OF PRESCRIBING INFORMATION

These highlights do not include all the information needed to use ZOLYMBUS™ safely and effectively. See full prescribing information for ZOLYMBUS™.
ZOLYMBUS™ (bimatoprost ophthalmic gel) 0.01%, for topical ophthalmic use
Initial U.S. Approval: 2001

1 INDICATIONS AND USAGE

ZOLYMBUS™ is a prostaglandin analog indicated for the reduction of elevated intraocular pressure in patients with open-angle glaucoma or ocular hypertension.

2 DOSAGE AND ADMINISTRATION

One drop in the affected eye(s) once daily in the evening.

3 DOSAGE FORMS AND STRENGTHS

Ophthalmic gel: 0.01% bimatoprost in a single-dose container.

4 CONTRAINDICATIONS

Hypersensitivity.

5 WARNINGS AND PRECAUTIONS

- Pigmentation: Pigmentation of the iris, periorbital tissue (eyelid) and eyelashes can occur. Iris pigmentation is likely to be permanent. (5.1)
- Eyelash Changes: Gradual change to eyelashes including increased length, thickness and number of lashes. Usually, reversible. (5.2)

6 ADVERSE REACTIONS

Most common adverse reactions (≥10%) are conjunctival hyperemia (14%) and eye irritation (11%). (6.1)

To report SUSPECTED ADVERSE REACTIONS, contact Thea Pharma Inc. at 1-833-838-4028 or FDA at 1-800-FDA-1088 or www.fda.gov/medwatch.

8 USE IN SPECIFIC POPULATIONS

Use in pediatric patients below the age of 16 years is not recommended because of potential safety concerns related to increased pigmentation following long-term chronic use. (8.4)

FULL PRESCRIBING INFORMATION

1 INDICATIONS AND USAGE

ZOLYMBUS™ is indicated for the reduction of elevated intraocular pressure (IOP) in patients with open-angle glaucoma or ocular hypertension.

2 DOSAGE AND ADMINISTRATION

The recommended dosage is one drop in the affected eye(s) once daily in the evening. ZOLYMBUS should not be administered more than once daily since it has been shown that more frequent administration of prostaglandin analogs may lessen the IOP lowering effect.

Reduction of the IOP starts approximately 4 hours after the first administration with maximum effect reached within approximately 8 to 12 hours.

ZOLYMBUS may be used concomitantly with other topical ophthalmic drug products to lower IOP. If more than one topical ophthalmic drug is being used, the drugs should be administered at least five (5) minutes apart.

If one dose is missed, treatment should continue with the next dose as normal.

The gel from one single-dose container is to be used immediately after opening for administration to one or both eyes. Since sterility cannot be maintained after the single-dose container is opened, discard the open container and the remaining contents immediately after administration.

3 DOSAGE FORMS AND STRENGTHS

Ophthalmic gel: 0.01% bimatoprost as a colorless, opalescent gel in a single-dose container.

4 CONTRAINDICATIONS

ZOLYMBUS is contraindicated in patients with hypersensitivity to bimatoprost or to any of the ingredients [see Adverse Reactions (6.2)] .

5 WARNINGS AND PRECAUTIONS

5.1 Pigmentation

Bimatoprost has been reported to cause changes to pigmented tissues. The most frequently reported changes have been increased pigmentation of the iris, periorbital tissue (eyelid) and eyelashes. Pigmentation is expected to increase as long as bimatoprost is administered. The pigmentation change is due to increased melanin content in the melanocytes rather than to an increase in the number of melanocytes. After discontinuation of bimatoprost, pigmentation of the iris is likely to be permanent, while pigmentation of the periorbital tissue and eyelash changes have been reported to be reversible in some patients. Patients who receive treatment should be informed of the possibility of increased pigmentation. The long term effects of increased pigmentation are not known.

Iris color change may not be noticeable for several months to years. Typically, the brown pigmentation around the pupil spreads concentrically towards the periphery of the iris and the entire iris or parts of the iris become more brownish. Neither nevi nor freckles of the iris appear to be affected by treatment. While treatment with ZOLYMBUS can be continued in patients who develop noticeably increased iris pigmentation, these patients should be examined regularly.

5.2 Eyelash Changes

ZOLYMBUS may gradually change eyelashes and vellus hair in the treated eye. These changes include increased length, thickness, and number of lashes. Eyelash changes are usually reversible upon discontinuation of treatment.

5.3 Intraocular Inflammation

Prostaglandin analogs, including bimatoprost, have been reported to cause intraocular inflammation. ZOLYMBUS should be used with caution in patients with active intraocular inflammation (e.g., iritis/uveitis) because inflammation may be exacerbated.

5.4 Macular Edema

Macular edema, including cystoid macular edema, has been reported during treatment with bimatoprost ophthalmic products. ZOLYMBUS should be used with caution in aphakic patients, in pseudophakic patients with a torn posterior lens capsule, or in patients with known risk factors for macular edema.

5.5 Contact Lens Use

Contact lenses should be removed prior to the administration of ZOLYMBUS and may be reinserted 15 minutes after administration.

6 ADVERSE REACTIONS

The following adverse reactions are described elsewhere in the labeling:

- Pigmentation including blepharal pigmentation and iris hyperpigmentation [see Warnings and Precautions (5.1)]
- Eyelash Changes [see Warnings and Precautions (5.2)]
- Intraocular Inflammation [see Warnings and Precautions (5.3)]
- Macular Edema [see Warnings and Precautions (5.4)]
- Hypersensitivity [see Contraindications (4)]

6.1 Clinical Trials Experience

Because clinical trials are conducted under widely varying conditions, adverse reaction rates observed in the clinical trials of a drug cannot be directly compared to rates in the clinical trials of another drug and may not reflect the rates observed in practice.

In the two clinical trials conducted with ZOLYMBUS (bimatoprost ophthalmic gel) 0.01% comparing it to preserved bimatoprost ophthalmic solution 0.01%, the most frequently reported ocular adverse reactions were conjunctival hyperemia (14%), eye irritation (11%), eye pruritus (9%) and foreign body sensation in eyes (8%). Other adverse drug reactions (reported in 1% to 6% of patients) with ZOLYMBUS in the studies included dry eye, abnormal sensation in eye, lacrimation increased, eye pain, and vision blurred.

6.2 Postmarketing Experience

The following adverse reactions have been identified during post-approval use of topical bimatoprost products. Because these reactions are reported voluntarily from a population of uncertain size, it is not always possible to reliably estimate their frequency or establish a causal relationship to drug exposure. These reactions, which have been chosen for inclusion due to either their seriousness, frequency of reporting, possible causal connection to bimatoprost, or a combination of these factors include: asthma-like symptoms, dizziness, dry eye, dyspnea, eye discharge, eye edema, foreign body sensation, headache, hypersensitivity including signs and symptoms of eye allergy and allergic dermatitis, hypertension, lacrimation increased, periorbital and lid changes associated with periorbital fat atrophy leading to skin tightness, deepening of the eyelid sulcus, eyelid ptosis, enophthalmos, and eyelid retraction; and photophobia.

8 USE IN SPECIFIC POPULATIONS

8.1 Pregnancy

Risk Summary
There are no adequate and well-controlled studies of ZOLYMBUS (bimatoprost ophthalmic gel) 0.01% administration in pregnant women. There is no increase in the risk of major birth defects or miscarriages based on bimatoprost post-marketing experience.

In embryofetal developmental studies, administration of bimatoprost to pregnant mice and rats during organogenesis, resulted in abortion and early delivery at oral doses at least 33 times (mice) or 94 times (rats) the human exposure to bimatoprost solution 0.03% dosed bilaterally once daily (based on blood area under the curve [AUC] levels). These adverse effects were not observed at 2.6 times (mice) and 47 times (rats) the human exposure to bimatoprost 0.03% dosed bilaterally once daily (based on blood AUC levels).

In pre/postnatal development studies, administration of bimatoprost to pregnant rats from organogenesis to the end of lactation resulted in reduced gestation length and fetal body weight, and increased fetal and pup mortality at oral doses at least 41 times the human systemic exposure to bimatoprost solution 0.03% dosed bilaterally once daily (based on blood AUC levels). No adverse effects were observed in rat offspring at exposures estimated at 14 times the human exposure to bimatoprost solution 0.03% dosed bilaterally once daily (based on blood AUC levels).

Because animal reproductive studies are not always predictive of human response ZOLYMBUS should be administered during pregnancy only if the potential benefit justifies the potential risk to the fetus.

The background risk of major birth defects and miscarriage for the indicated population is unknown. However, the background risk in the U.S. general population of major birth defects is 2 to 4%, and of miscarriage is 15 to 20%, of clinically recognized pregnancies.

Data
Animal Data
In an embryofetal development rat study, abortion was observed in pregnant rats administered bimatoprost orally during organogenesis at 0.6 mg/kg/day (94 times the human systemic exposure to bimatoprost solution 0.03% dosed bilaterally once daily, based on AUC). The No Observed Adverse Effect Level (NOAEL) for abortion was 0.3 mg/kg/day (estimated at 47 times the human systemic exposure to bimatoprost solution 0.03% dosed bilaterally once daily, based on AUC). No abnormalities were observed in rat fetuses at doses up to 0.6 mg/kg/day.

In an embryofetal development mouse study, abortion and early delivery were observed in pregnant mice administered bimatoprost orally during organogenesis at doses greater than or equal to 0.3 mg/kg/day (33 times the human systemic exposure to bimatoprost solution 0.03% dosed bilaterally once daily, based on AUC). The NOAEL for abortion and early delivery was 0.1 mg/kg/day (2.6 times the human systemic exposure to bimatoprost solution 0.03% dosed bilaterally once daily, based on AUC). No abnormalities were observed in mouse fetuses at doses up to 0.6 mg/kg/day (72 times the human systemic exposure to bimatoprost solution 0.03% dosed bilaterally once daily based on AUC).

In a pre/postnatal development study, treatment of pregnant rats with bimatoprost orally from gestation day 7 to lactation day 20 resulted in reduced gestation length, increased late resorptions, fetal deaths, and postnatal pup mortality, and reduced pup body weight at doses greater than or equal to 0.3 mg/kg/day. These effects were observed at exposures at least 41 times the human systemic exposure to bimatoprost solution 0.03% dosed bilaterally once daily, based on AUC. The NOAEL for postnatal development and mating performance of the offspring was 0.1 mg/kg/day (estimated at 14 times the human systemic exposure to bimatoprost solution 0.03% dosed bilaterally once daily, based on AUC).

8.2 Lactation

Risk Summary
It is not known whether topical ocular treatment with ZOLYMBUS could result in sufficient systemic absorption to produce detectable quantities in human milk. In animal studies, bimatoprost has been shown to be present in breast milk of lactating rats at an intravenous dose (i.e., 1 mg/kg) 970 times the recommended human ophthalmic dose (on a mg/m^2basis), however, no animal data is available at clinically relevant doses.

The developmental and health benefits of breastfeeding should be considered along with the mother’s clinical need for ZOLYMBUS and any potential adverse effects on the breastfed child from ZOLYMBUS.

8.4 Pediatric Use

Use in pediatric patients below the age of 16 years is not recommended because of potential safety concerns related to increased pigmentation following long-term chronic use.

8.5 Geriatric Use

No overall differences in safety or effectiveness have been observed between elderly and other adult patients.

10 OVERDOSAGE

No information is available on overdosage in humans. If overdose with ZOLYMBUS occurs, treatment should be symptomatic.

In oral (by gavage) mouse and rat studies, doses up to 100 mg/kg/day did not produce any toxicity. This dose expressed as mg/m^2is at least 90 times higher than the accidental dose of the entire content of a pack of ZOLYMBUS (30 x 0.3 g single-dose containers; 9 g) for a 10 kg child.

11 DESCRIPTION

ZOLYMBUS contains bimatoprost, a synthetic prostamide analog with ocular hypotensive activity, for topical ophthalmic use. The chemical name is 5-Heptenamide, 7-[(1R,2R,3R,5S)-3,5-dihydroxy-2- [(1E,3S)-3-hydroxy-5-phenyl-1-penten-1-yl]cyclopentyl]-N-ethyl, (5Z)-, with the molecular weight 415.58 and molecular formula is C25H37NO4. Its chemical structure is:

Bimatoprost is a crystalline powder, which is very soluble in ethyl alcohol and methyl alcohol and slightly soluble in water. ZOLYMBUS is a sterile, colorless, opalescent ophthalmic gel with an osmolality of approximately 300 mOsmol/kg.

Each container contains 0.03 mg of bimatoprost and the following inactive ingredients: carbomer, polyethylene glycol, sodium acetate trihydrate, sorbitol, sodium hydroxide and water for injection with a pH range from 6.9 to 7.9.

ZOLYMBUS does not contain a preservative.

12 CLINICAL PHARMACOLOGY

12.1 Mechanism of Action

Bimatoprost, a prostaglandin analog, is a synthetic structural analog of prostaglandin with ocular hypotensive activity. It selectively mimics the effects of naturally occurring substances, prostamides. Bimatoprost is believed to lower intraocular pressure (IOP) in humans by increasing outflow of aqueous humor through both the trabecular meshwork and uveoscleral routes. Elevated IOP presents a major risk factor for glaucomatous field loss. The higher the level of IOP, the greater the likelihood of optic nerve damage and visual field loss.

12.3 Pharmacokinetics

Absorption
After one drop of bimatoprost ophthalmic gel 0.01% was administered once daily to both eyes of 20 healthy participants for two weeks, blood concentrations peaked within 10 minutes after dosing and were below the lower limit of detection (5 pg/mL) in most subjects within 30 minutes after dosing. Mean Cmaxvalues were similar on days 1 and 14 at 0.021 ng/mL and 0.028 ng/mL, respectively, indicating that a steady state was reached. There was no significant systemic drug accumulation over time.

Distribution
Bimatoprost is moderately distributed into body tissues with a steady-state volume of distribution of 0.67 L/kg. In human blood, bimatoprost resides mainly in the plasma. Approximately 12% of bimatoprost remains unbound in human plasma.

Elimination
Metabolism
Bimatoprost is the major circulating species in the blood once it reaches the systemic circulation following ocular dosing. Bimatoprost then undergoes oxidation, N-deethylation and glucuronidation to form a diverse variety of metabolites.

Excretion
Following an intravenous dose of radiolabeled bimatoprost (3.12 mcg/kg) to six healthy subjects, the maximum blood concentration of unchanged drug was 12.2 ng/mL and decreased rapidly with an elimination half-life of approximately 45 minutes. The total blood clearance of bimatoprost was 1.5 L/hr/kg. Up to 67% of the administered dose was excreted in the urine while 25% of the dose was recovered in the feces.

13 NONCLINICAL TOXICOLOGY

13.1 Carcinogenesis, Mutagenesis, Impairment of Fertility

Carcinogenesis
Bimatoprost was not carcinogenic in either mice or rats when administered by oral gavage for 104 weeks at doses up to 2 mg/kg/day and 1 mg/kg/day, respectively (192 and 291 times the estimated human systemic exposure to bimatoprost solution 0.03% dosed bilaterally once daily, respectively, based on blood AUC levels).

Mutagenesis
Bimatoprost was not mutagenic or clastogenic in the Ames test, in the mouse lymphoma test, or in the in vivo mouse micronucleus tests.

Impairment of Fertility
Bimatoprost did not impair fertility in male or female rats up to doses of 0.6 mg/kg/day (at least 103 times the recommended human exposure to bimatoprost solution 0.03% dosed bilaterally once daily based on blood AUC levels).

14 CLINICAL STUDIES

In a 12-week clinical trial of patients with open-angle glaucoma or ocular hypertension with a mean baseline IOP of 23 to 24 mmHg, the IOP-lowering effect of ZOLYMBUS once daily (in the evening) was non-inferior to preserved bimatoprost ophthalmic solution 0.01%.

16 HOW SUPPLIED/STORAGE AND HANDLING

ZOLYMBUS (bimatoprost ophthalmic gel) 0.01% is supplied as a colorless, opalescent gel in blow-fill-seal single-dose container packaged in foil pouches.
10 single-dose containers per pouch.

NDC 82584-010-30; Carton of 30 single-dose containers

Storage:

Store at 20°C to 30°C (68°F to 86°F).

Protect from light. Store in the original pouch. After the pouch is opened, the single-dose containers may be stored in the opened foil pouch for up to 14 days at 20°C to 30°C (68°F to 86°F).
Patient should be advised to write down the date the foil pouch is opened in the space provided on the pouch.
Discard any unused containers 14 days after first opening the pouch.

Single-dose container. Discard unused portion.

17 PATIENT COUNSELING INFORMATION

Advise the patient to read the FDA-approved patient labeling (Patient Information and Instructions for Use).

Potential for Pigmentation
Advise patients about the potential for increased brown pigmentation of the iris, which may be permanent. Also inform patients about the possibility of eyelid skin darkening, which may be reversible after discontinuation of ZOLYMBUS (bimatoprost ophthalmic gel).

Potential for Eyelash Changes
Inform patients of the possibility of eyelash and vellus hair changes in the treated eye during treatment with ZOLYMBUS. These changes may result in a disparity between eyes in length, thickness, pigmentation, number of eyelashes or vellus hairs, and/or direction of eyelash growth. Eyelash changes are usually reversible upon discontinuation of treatment.

Handling the Container
Advise patients that ZOLYMBUS is a sterile gel that does not contain a preservative. The drops are supplied in a single-dose container. The gel from one single-dose container is to be used immediately after opening for administration to one or both eyes. Since sterility cannot be maintained after the single-dose container is opened, discard the open container and the remaining contents immediately after administration. Open a new single-dose container every time you use ZOLYMBUS.

When to Seek Physician Advice
Advise patients that if they develop an intercurrent ocular condition (e.g., trauma or infection), have ocular surgery, or develop any ocular reactions, particularly conjunctivitis and eyelid reactions, they should immediately seek their physician’s advice concerning the continued use of ZOLYMBUS.

Contact Lens Use
Advise patients that contact lenses should be removed prior to administration of ZOLYMBUS. Lenses may be reinserted 15 minutes following administration of ZOLYMBUS.

Use with Other Ophthalmic Drugs
Advise patients that if more than one topical ophthalmic drug is being used, the drugs should be administered at least five (5) minutes apart.

If a Dose is Missed
Advise patients that if one dose is missed, treatment should continue with the next dose as normal.

Manufactured for: Thea Pharma Inc.Waltham, MA 02451.
U.S. Patent N°. 10,314,780. ©2025, Laboratoires Théa. All rights reserved. ZOLYMBUS™ is a trademark of Laboratoires Théa.

PATIENT INFORMATION
ZOLYMBUSTM(zoh LIM bus)
(bimatoprost ophthalmic gel 0.01%)
for topical ophthalmic use

What is ZOLYMBUS?
ZOLYMBUS is a prescription eye gel used to lower the pressure in the eye (intraocular pressure) in people with open-angle glaucoma or ocular hypertension when their eye pressure is too high. ZOLYMBUS belongs to a group of medicines called prostaglandin analogs.
ZOLYMBUS is not recommended in children younger than 16 years of age because of the potential for eye and eyelid color changes.

Do not use ZOLYMBUS ifyou are allergic to bimatoprost or any of the ingredients in ZOLYMBUS. See the end of this Patient Information leaflet for a complete list of ingredients in ZOLYMBUS.

Before using ZOLYMBUS, tell your healthcare provider about all your medical conditions, including if you:

- have or have had eye problems including any surgery on your eye or eyes
- are using any other eye medicines
- are pregnant or plan to become pregnant. It is not known if ZOLYMBUS will harm your unborn baby. If you become pregnant while using ZOLYMBUS talk to your healthcare provider right away.
- are breastfeeding or plan to breastfeed. It is not known if ZOLYMBUS passes into your breast milk. Talk to your healthcare provider about the best way to feed your baby if you use ZOLYMBUS.

Tell your healthcare provider about all the medicines you take, including prescription and over-the-counter medicines, vitamins, and herbal supplements.
Know the medicines you take. Keep a list of them to show your healthcare provider and pharmacist when you get a new medicine.

How should I use ZOLYMBUS?
Read the Instructions for Use at the end of this Patient Information leaflet for additional instructions about the right way to use ZOLYMBUS.

- Use 1 drop of ZOLYMBUS in your affected eye or eyes each evening.Talk to your healthcare provider or pharmacist if you are not sure how to use ZOLYMBUS.
- Your ZOLYMBUS may not work as well if you use it more than 1 time each evening.
- If you miss a dose of ZOLYMBUS, skip the missed dose and use the next dose at your regular time.
- If you use other medicines in your eye, wait at least 5 minutes between using ZOLYMBUS and your other eye medicines.
- Contact lenses should be taken out before using ZOLYMBUS and you should wait at least 15 minutes after giving the dose of ZOLYMBUS before putting the contact lenses back into your eyes.
- Use your ZOLYMBUS right away after opening for use in 1 or both eyes. Each ZOLYMBUS single-dose container is sterile and is to be used 1 time then thrown away. Do not save any ZOLYMBUS that may be left over after you use your medicine. Using ZOLYMBUS that is not sterile may cause other eye problems.

What are the possible side effects of ZOLYMBUS?
ZOLYMBUS may cause serious side effects including:

- changes in the color of your eye (iris).Your iris may become more brown in color while using ZOLYMBUS. This color change may not go away when you stop using ZOLYMBUS. If ZOLYMBUS is used in 1 eye only, the color of that eye may always be a different color from the color of your other eye.
- darkening of the color of the skin around your eye (eyelid).These skin changes usually go away when you stop using ZOLYMBUS.
- increasing the length, thickness, color, and number of your eyelashes.These eyelash changes usually go away when you stop using ZOLYMBUS.
- hair growth on skin around the treated eye.This hair growth usually goes away when you stop using ZOLYMBUS.
- inner eye swelling(inflammation). Swelling or thickening may occur in the center of your eye (macular edema) and swelling in the middle layer of your eye (uvea, intraocular inflammation). Tell your healthcare provider if you experience eye inflammation or have a known risk of macular edema.

The most common side effects of ZOLYMBUS include:

- redness of and around the eye (conjunctival hyperemia)
- eye irritation
- itchy eyes (eye pruritus)
- dry eye

- foreign body sensation in the eyes
- increase of tears in the eye (increased lacrimation)
- eye pain
- blurry vision

Tell your healthcare provider right away if you have any new eye problems while using ZOLYMBUS, including:
• an eye injury

• an eye infection
• eye surgery
• swelling and redness of and around your eye (conjunctivitis)
• problems with your eyelids

Additionally, the following side effects have been reported in other bimatoprost medicines like ZOLYMBUS, when used in the eye (topical use):
• asthma-like symptoms
• dizziness
• shortness of breath (dyspnea)
• eye discharge (eye mucus)
• inflammation of the eye (eye edema)
• headache
• signs and symptoms of eye allergy and allergic inflammation of the skin (allergic dermatitis)
• hypertension
• periorbital and lid changes associated with loss of fat leading to skin tightness
• deepening of the eyelid crease (eyelid sulcus)
• drooping eyelid (eyelid ptosis)
• sunken eye (enophtalmos)
• eyelid retraction
• sensitivity to light (photophobia)

Tell your healthcare provider if you have any side effect that bothers you or does not go away.

These are not all the possible side effects of ZOLYMBUS. For more information, ask your healthcare provider or pharmacist.
Call your doctor for medical advice about side effects. You may report side effects to FDA at 1-800-FDA- 1088.

How should I store ZOLYMBUS?
Before opening the foil pouches:
• Keep the ZOLYMBUS single-dose containers in their original foil pouch. Protect from light.

• Store the unopened foil pouches between 68°F to 86°F (20°C to 30°C).
• Do not open the foil pouch containing ZOLYMBUS until you are ready to use the eye drops.
After opening the foil pouch:
• Store the single-dose containers in the opened foil pouch between 68°F to 86°F (20°C to 30°C), for up to 14 days.
• Write down the date of first opening the foil pouch in the space provided on the pouch.
• Throw away all unused ZOLYMBUS single-dose containers in the opened foil pouch after 14 days.
Keep ZOLYMBUS and all medicines out of the reach of children.

General information about the safe and effective use of ZOLYMBUS.
Medicines are sometimes prescribed for purposes other than those listed in a Patient Information leaflet. Do not use ZOLYMBUS for a condition for which it was not prescribed. Do not give ZOLYMBUS to other people, even if they have the same symptoms that you have. It may harm them.
You can ask your pharmacist or healthcare provider for information about ZOLYMBUS that is written for health professionals.

What are the ingredients in ZOLYMBUS?

Active ingredients:bimatoprost
Inactive ingredients:carbomer, polyethylene glycol, sodium acetate trihydrate, sorbitol, sodium hydroxide and water.

ZOLYMBUS does not contain a preservative.

Manufactured for: Thea Pharma Inc.Waltham, MA 02451.

U.S. Patent N°. 10,314,780. ©2025, Laboratoires Théa. All rights reserved. ZOLYMBUS™ is a trademark of Laboratoires Théa.

This Patient Information has been approved by the U.S. Food and Drug Administration.

Approved: 09/2025

Instructions for Use ZOLYMBUS™ (zoh LIM bus) (bimatoprost ophthalmic gel) 0.01% for topical ophthalmic use
Read this Instructions for Use before using your ZOLYMBUS™ and each time you get a refill. There may be new information. This leaflet does not take the place of talking with your healthcare provider about your medical condition or your treatment.
Important Information You Need to Know Before Using ZOLYMBUS:; - ZOLYMBUS is for use in the eye. Do not swallow ZOLYMBUS. - ZOLYMBUS single-dose containers are packaged in a foil pouch. - Do notuse the ZOLYMBUS single-dose containers if the foil pouch is already opened when you receive it. - Write down the date you open the foil pouch in the space provided on the pouch. - Use 1 drop of ZOLYMBUS in your affected eye or eyes each evening. - If you use other eye medicines dropped into the eye (topically applied ophthalmic medicines), use the medicines at least 5 minutes before or 5 minutes after the use of ZOLYMBUS. - Do notopen the ZOLYMBUS single-dose container until you are ready to use the eye drops.
Please follow these instructions to use ZOLYMBUS:
Step 1. | Wash your hands and sit or stand comfortably.
Step 2. | - Open the foil pouch containing a strip of 10 single-dose containers. - Write down the date of first opening on the foil pouch.
Step 3. | - Take the strip of single-dose containers from the foil pouch. - Break off 1 single-dose container from the strip. - Place the remaining strip of unopened single-dose containers back in the foil pouch and fold the edge to close the pouch.
Step 4. | - Hold the single-dose container upright. - Make sure that your ZOLYMBUS medicine is in the bottom part of the single-dose container. - Twist open the top of the single-dose container as shown. Do not touch the tip after opening the container.
Step 5. | - Tilt your head backwards. If you are unable to tilt your head, lie down. - Use your finger to gently pull down the lower eyelid of your affected eye.
Step 6. | Place the tip of the single-dose container close to, but not touching your eye.
Step 7. | Squeeze the single-dose container gently so that only 1 drop goes into your eye, then release the lower eyelid. If the drop misses your eye completely, try again.
- If your healthcare provider has told you to use ZOLYMBUS drops in both eyes, repeat Step 5 to Step 7 for your other eye.
- Each single-dose container contains enough drops for both eyes.
- Throw away the single-dose container after use. Do not keep it to use it again even if there is product left in the container.To lessen the chance of infection, a new single-dose container must be opened each time you are ready to use ZOLYMBUS.
- Place the folded foil pouch back in the carton. The unopened single-dose containers must be used within 14 days after opening the foil pouch. Protect from light.
Manufactured for: Thea Pharma Inc.Waltham, MA 02451.
U.S. Patent N°. 10,314,780. ©2025, Laboratoires Théa. All rights reserved. ZOLYMBUS™ is a trademark of Laboratoires Théa.
This Patient Information and Instructions for Use have been approved by the U.S. Food and Drug Administration. |  | Approved: 09/2025

PRINCIPAL DISPLAY PANEL -ophthalmic gel 0.01%; Carton of 30 single-dose containers

NDC 82584-010-30

ZOLYMBUS™

(bimatoprost ophthalmic gel)

0.01%

Contains:

Active:bimatoprost 0.1 mg/g.

Inactive ingredients:carbomer, sodium acetate

trihydrate, polyethylene glycol, sodium hydroxide (for

pH adjustment), sorbitol and water for injection.

Recommended Dosage:one drop in the affected eye(s)

once daily in the evening.

Single-dose container. Discard unused portion.

Storage:Store at 20°C to 30°C (68°F to 86°F).

See Prescribing Information.

30 single-dose containers: 3 pouches x 10 single-dose

containers (0.3 g each).

Store in the original pouch. After the pouch is opened, the

single-dose containers may be stored in the opened foil

pouch for up to 14 days.

Discard any unused containers 14 days after first

opening the pouch.

Manufactured for Thea Pharma Inc.

Waltham, MA 02451

U.S. Patent N°. 10,314,780. ©2024, Laboratoires Théa.

All rights reserved. ZOLYMBUS™ is a trademark of

Laboratoires Théa.

Théa Logo

PRINCIPAL DISPLAY PANEL - ophthalmic gel 0.01%; Pouch of 10 single-dose containers

NDC 82584-010-81

Recommended Dosage:one drop in the affected eye(s) once daily in the evening.
Single-dose container. Discard unused portion.
See carton for inactive ingredients.
Storage:Store at 20°C to 30°C (68°F to 86°F).
Protect from light. Store in the original pouch. After the pouch is opened, the single-use containers may be stored in the
opened foil pouch for up to 14 days.
Discard any unused containers 14 days after first opening the pouch.
Write down the date you open the pouch. __ / __ / __

ZOLYMBUS™
(bimatoprost ophthalmic gel) 0.01%
For Topical Ophthalmic Use
10 single-dose containers (0.3 g each)
Rx only
Sterile - Contains no preservatives
Manufactured for Thea Pharma Inc.
Waltham, MA 02451

Théa Logo

Lot:

EXP: